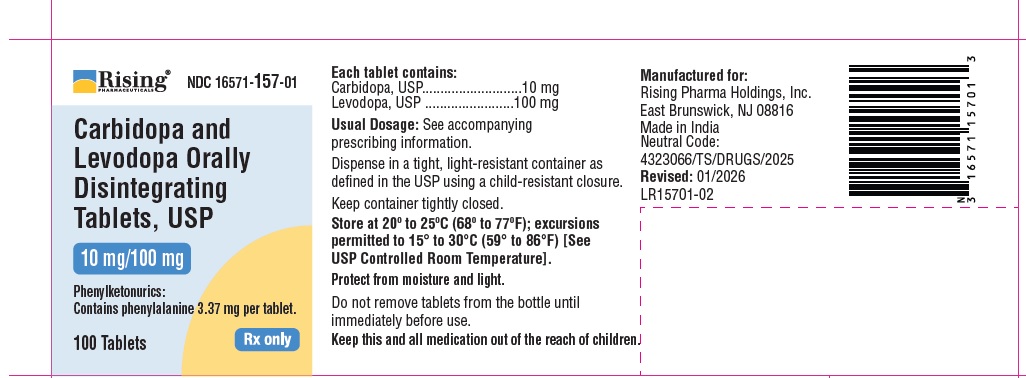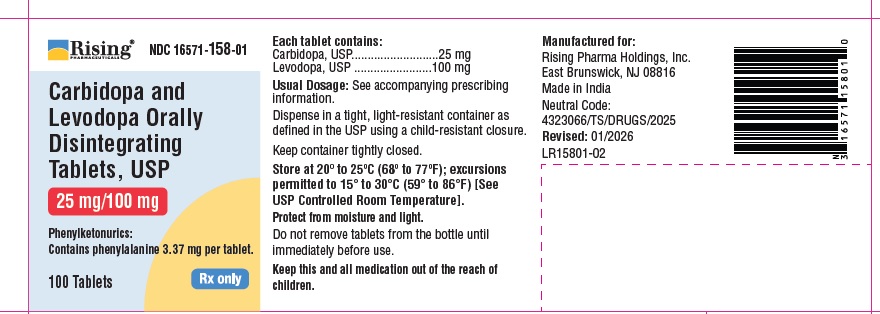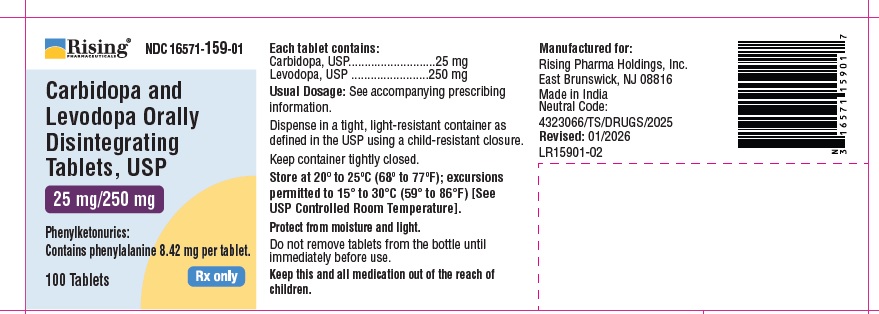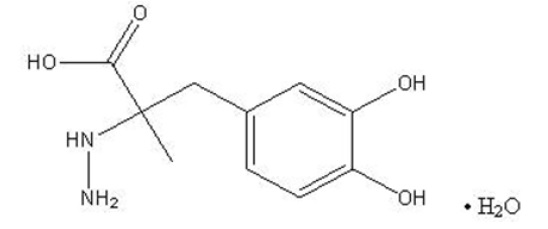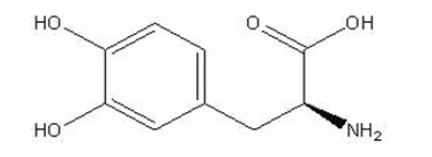 DRUG LABEL: Carbidopa and Levodopa
NDC: 16571-157 | Form: TABLET, ORALLY DISINTEGRATING
Manufacturer: Rising Pharma Holdings, Inc.
Category: prescription | Type: HUMAN PRESCRIPTION DRUG LABEL
Date: 20260127

ACTIVE INGREDIENTS: CARBIDOPA 10 mg/1 1; LEVODOPA 100 mg/1 1
INACTIVE INGREDIENTS: ASPARTAME; CROSPOVIDONE, UNSPECIFIED; MANNITOL; MICROCRYSTALLINE CELLULOSE 101; SILICON DIOXIDE; SODIUM STEARYL FUMARATE; SORBITOL; FD&C BLUE NO. 1 ALUMINUM LAKE; D&C YELLOW NO. 10 ALUMINUM LAKE

Carbidopa and Levodopa Orally Disintegrating Tablets, USP 10 mg/100 mg, 25 mg/100 mg and 25 mg/250 mg
Rx only

DESCRIPTION

Carbidopa and levodopa orally disintegrating tablets, USP are a combination of carbidopa and levodopa for the treatment of Parkinson's disease and syndrome. Carbidopa and levodopa orally disintegrating tablets are an orally administered formulation of carbidopa and levodopa which rapidly disintegrates on the tongue and does not require water to aid dissolution or swallowing.

Carbidopa, USP, an inhibitor of aromatic amino acid decarboxylation, is a white to creamy white powder, slightly soluble in water, with a molecular weight of 244.2. It is designated chemically as (-)-L-α-Hydrazino-3,4-dihydroxy-α-methylhydrocinnamic acid monohydrate. Its molecular formula is C10H14N2O4•H2O, and its structural formula is:

Tablet content is expressed in terms of anhydrous carbidopa which has a molecular weight of 226.2.

Levodopa, USP, an aromatic amino acid, is a white to off-white, odorless crystalline powder, slightly soluble in water, with a molecular weight of 197.2. It is designated chemically as (-)-3-(3,4-Dihydroxyphenyl)-L-alanine. Its molecular formula is C9H11NO4, and its structural formula is:

Carbidopa and levodopa orally disintegrating tablets, USP are supplied as tablets in three strengths:

Carbidopa and Levodopa Orally Disintegrating Tablets 10 mg /100 mg, containing 10 mg of carbidopa and 100 mg of levodopa.

Carbidopa and Levodopa Orally Disintegrating Tablets 25 mg/100 mg, containing 25 mg of carbidopa and 100 mg of levodopa.

Carbidopa and Levodopa Orally Disintegrating Tablets 25 mg/250 mg, containing 25 mg of carbidopa and 250 mg of levodopa.

Inactive ingredients are aspartame, crospovidone, mannitol, microcrystalline cellulose, peppermint flavor, silica, sodium stearyl fumarate and sorbitol. In addition, the 25 mg/100 mg tablets contain FD&C Blue No. 1 Aluminum Lake and the 10 mg/100 mg and 25 mg/250 mg tablets contain D&C Yellow No. 10 Aluminum Lake and FD&C Blue No. 1 Aluminum Lake.

CLINICAL PHARMACOLOGY

Mechanism of Action

Parkinson’s disease is a progressive, neurodegenerative disorder of the extrapyramidal nervous system affecting the mobility and control of the skeletal muscular system. Its characteristic features include resting tremor, rigidity, and bradykinetic movements. Symptomatic treatments, such as levodopa therapies, may permit the patient better mobility.

Current evidence indicates that symptoms of Parkinson’s disease are related to depletion of dopamine in the corpus striatum. Administration of dopamine is ineffective in the treatment of Parkinson’s disease apparently because it does not cross the blood-brain barrier. However, levodopa, the metabolic precursor of dopamine, does cross the blood-brain barrier, and presumably is converted to dopamine in the brain. This is thought to be the mechanism whereby levodopa relieves symptoms of Parkinson’s disease.

Pharmacodynamics

When levodopa is administered orally, it is rapidly decarboxylated to dopamine in extracerebral tissues so that only a small portion of a given dose is transported unchanged to the central nervous system. For this reason, large doses of levodopa are required for adequate therapeutic effect, and these may often be accompanied by nausea and other adverse reactions, some of which are attributable to dopamine formed in extracerebral tissues.

Since levodopa competes with certain amino acids for transport across the gut wall, the absorption of levodopa may be impaired in some patients on a high protein diet.

Carbidopa inhibits decarboxylation of peripheral levodopa. It does not cross the blood-brain barrier and does not affect the metabolism of levodopa within the central nervous system.

The incidence of levodopa-induced nausea and vomiting is less with carbidopa and levodopa than with levodopa. In many patients, this reduction in nausea and vomiting will permit more rapid dosage titration.

Since its decarboxylase inhibiting activity is limited to extracerebral tissues, administration of carbidopa with levodopa makes more levodopa available for transport to the brain.

Pharmacokinetics

Carbidopa reduces the amount of levodopa required to produce a given response by about 75% and, when administered with levodopa, increases both plasma levels and the plasma half-life of levodopa, and decreases plasma and urinary dopamine and homovanillic acid.

The plasma half-life of levodopa is about 50 minutes, without carbidopa. When carbidopa and levodopa are administered together, the half-life of levodopa is increased to about 1.5 hours. At steady state, the bioavailability of carbidopa from carbidopa and levodopa orally disintegrating tablet is approximately 99% relative to the concomitant administration of carbidopa and levodopa.

In clinical pharmacologic studies, simultaneous administration of carbidopa and levodopa produced greater urinary excretion of levodopa in proportion to the excretion of dopamine than administration of the two drugs at separate times.

Pyridoxine hydrochloride (vitamin B6), in oral doses of 10 mg to 25 mg, may reverse the effects of levodopa by increasing the rate of aromatic amino acid decarboxylation. Carbidopa inhibits this action of pyridoxine; therefore, carbidopa and levodopa orally disintegrating tablets can be given to patients receiving supplemental pyridoxine (vitamin B6).

Special Populations

Geriatric: A study in eight young healthy subjects (21 to 22 yr) and eight elderly healthy subjects (69 to 76 yr) showed that the absolute bioavailability of levodopa was similar between young and elderly subjects following oral administration of levodopa and carbidopa. However, the systemic exposure (AUC) of levodopa was increased by 55% in elderly subjects compared to young subjects. Based on another study in forty patients with Parkinson’s disease, there was a correlation between age of patients and the increase of AUC of levodopa following administration of levodopa and an inhibitor of peripheral dopa decarboxylase. AUC of levodopa was increased by 28% in elderly patients (≥ 65 yr) compared to young patients (< 65 yr). Additionally, mean value of Cmax for levodopa was increased by 24% in elderly patients (≥ 65 yr) compared to young patients (< 65 yr) (see PRECAUTIONS, Geriatric Use).

The AUC of carbidopa was increased in elderly subjects (n=10, 65 to 76 yr) by 29% compared to young subjects (n=24, 23 to 64 yr) following IV administration of 50 mg levodopa with carbidopa (50 mg). This increase is not considered a clinically significant impact.

INDICATIONS AND USAGE

Carbidopa and levodopa orally disintegrating tablets are indicated in the treatment of Parkinson’s disease, post-encephalitic parkinsonism, and symptomatic parkinsonism that may follow carbon monoxide intoxication or manganese intoxication.

Carbidopa allows patients treated for Parkinson’s disease to use much lower doses of levodopa. Some patients who responded poorly to levodopa have improved on carbidopa and levodopa orally disintegrating tablets. This is most likely due to decreased peripheral decarboxylation of levodopa caused by administration of carbidopa rather than by a primary effect of carbidopa on the nervous system. Carbidopa has not been shown to enhance the intrinsic efficacy of levodopa.

Carbidopa may also reduce nausea and vomiting and permit more rapid titration of levodopa.

CONTRAINDICATIONS

Nonselective monoamine oxidase (MAO) inhibitors are contraindicated for use with carbidopa and levodopa orally disintegrating tablets. These inhibitors must be discontinued at least two weeks prior to initiating therapy with carbidopa and levodopa orally disintegrating tablets. Carbidopa and levodopa orally disintegrating tablets may be administered concomitantly with the manufacturer’s recommended dose of an MAO inhibitor with selectivity for MAO type B (e.g., selegiline HCl) (see PRECAUTIONS, Drug Interactions).

Carbidopa and levodopa orally disintegrating tablets are contraindicated in patients with known hypersensitivity to any component of this drug, and in patients with narrow-angle glaucoma.

WARNINGS

When carbidopa and levodopa orally disintegrating tablets are to be given to patients who are being treated with levodopa, levodopa must be discontinued at least twelve hours before therapy with carbidopa and levodopa orally disintegrating tablets are started. In order to reduce adverse reactions, it is necessary to individualize therapy. See DOSAGE AND ADMINISTRATION section before initiating therapy.

The addition of carbidopa with levodopa in the form of carbidopa and levodopa orally disintegrating tablets reduces the peripheral effects (nausea, vomiting) due to decarboxylation of levodopa; however, carbidopa does not decrease the adverse reactions due to the central effects of levodopa. Because carbidopa permits more levodopa to reach the brain and more dopamine to be formed, certain adverse central nervous system (CNS) effects, e.g., dyskinesias (involuntary movements), may occur at lower dosages and sooner with carbidopa and levodopa orally disintegrating tablets than with levodopa alone.

All patients should be observed carefully for the development of depression with concomitant suicidal tendencies.

Carbidopa and levodopa orally disintegrating tablets should be administered cautiously to patients with severe cardiovascular or pulmonary disease, bronchial asthma, renal, hepatic or endocrine disease.

As with levodopa, care should be exercised in administering carbidopa and levodopa orally disintegrating tablets to patients with a history of myocardial infarction who have residual atrial, nodal, or ventricular arrhythmias. In such patients, cardiac function should be monitored with particular care during the period of initial dosage adjustment, in a facility with provisions for intensive cardiac care.

As with levodopa, treatment with carbidopa and levodopa orally disintegrating tablets may increase the possibility of upper gastrointestinal hemorrhage in patients with a history of peptic ulcer.

Falling Asleep During Activities of Daily Living and Somnolence

Patients taking carbidopa and levodopa orally disintegrating tablets alone or with other dopaminergic drugs have reported suddenly falling asleep without prior warning of sleepiness while engaged in activities of daily living (includes operation of motor vehicles). Road traffic accidents attributed to sudden sleep onset have been reported. Although many patients reported somnolence while on dopaminergic medications, there have been reports of road traffic accidents attributed to sudden onset of sleep in which the patient did not perceive any warning signs, such as excessive drowsiness, and believed that they were alert immediately prior to the event. Sudden onset of sleep has been reported to occur as long as one year after the initiation of treatment.

Falling asleep while engaged in activities of daily living usually occurs in patients experiencing pre-existing somnolence, although some patients may not give such a history. For this reason, prescribers should reassess patients for drowsiness or sleepiness especially since some of the events occur well after the start of treatment. Prescribers should be aware that patients may not acknowledge drowsiness or sleepiness until directly questioned about drowsiness or sleepiness during specific activities. Patients should be advised to exercise caution while driving or operating machines during treatment with carbidopa and levodopa orally disintegrating tablets. Patients who have already experienced somnolence or an episode of sudden sleep onset should not participate in these activities during treatment with carbidopa and levodopa orally disintegrating tablets.

Before initiating treatment with carbidopa and levodopa orally disintegrating tablets, advise patients about the potential to develop drowsiness and ask specifically about factors that may increase the risk for somnolence with carbidopa and levodopa orally disintegrating tablets such as the use of concomitant sedating medications and the presence of sleep disorders. Consider discontinuing carbidopa and levodopa orally disintegrating tablets in patients who report significant daytime sleepiness or episodes of falling asleep during activities that require active participation (e.g., conversations, eating, etc.). If treatment with carbidopa and levodopa orally disintegrating tablets continues, patients should be advised not to drive and to avoid other potentially dangerous activities that might result in harm if the patients become somnolent. There is insufficient information to establish that dose reduction will eliminate episodes of falling asleep while engaged in activities of daily living.

Hyperpyrexia and Confusion

Sporadic cases of a symptom complex resembling neuroleptic malignant syndrome (NMS) have been reported in association with dose reductions or withdrawal of certain antiparkinsonian agents such as levodopa, carbidopa and levodopa, or carbidopa and levodopa extended release. Therefore, patients should be observed carefully when the dosage of levodopa is reduced abruptly or discontinued, especially if the patient is receiving neuroleptics.

NMS is an uncommon but life-threatening syndrome characterized by fever or hyperthermia. Neurological findings, including muscle rigidity, involuntary movements, altered consciousness, mental status changes; other disturbances, such as autonomic dysfunction, tachycardia, tachypnea, sweating, hyper- or hypotension; laboratory findings, such as creatine phosphokinase elevation, leukocytosis, myoglobinuria, and increased serum myoglobin have been reported.

The early diagnosis of this condition is important for the appropriate management of these patients. Considering NMS as a possible diagnosis and ruling out other acute illnesses (e.g., pneumonia, systemic infection, etc.) is essential. This may be especially complex if the clinical presentation includes both serious medical illness and untreated or inadequately treated extrapyramidal signs and symptoms (EPS). Other important considerations in the differential diagnosis include central anticholinergic toxicity, heat stroke, drug fever, and primary central nervous system (CNS) pathology.

The management of NMS should include: 1) intensive symptomatic treatment and medical monitoring and 2) treatment of any concomitant serious medical problems for which specific treatments are available. Dopamine agonists, such as bromocriptine, and muscle relaxants, such as dantrolene, are often used in the treatment of NMS; however, their effectiveness has not been demonstrated in controlled studies.

PRECAUTIONS

General

As with levodopa, periodic evaluations of hepatic, hematopoietic, cardiovascular, and renal function are recommended during extended therapy.
Patients with chronic wide-angle glaucoma may be treated cautiously with carbidopa and levodopa orally disintegrating tablets provided the intraocular pressure is well-controlled and the patient is monitored carefully for changes in intraocular pressure during therapy.

Dyskinesia
Levodopa alone, as well as carbidopa and levodopa orally disintegrating tablets, are associated with dyskinesias. The occurrence of dyskinesias may require dosage reduction.

Hallucinations / Psychotic-Like Behavior
Hallucinations and psychotic-like behavior have been reported with dopaminergic medications. In general, hallucinations present shortly after the initiation of therapy and may be responsive to dose reduction in levodopa. Hallucinations may be accompanied by confusion and to a lesser extent sleep disorder (insomnia) and excessive dreaming.

Carbidopa and levodopa orally disintegrating tablets may have similar effects on thinking and behavior. This abnormal thinking and behavior may present with one or more symptoms, including paranoid ideation, delusions, hallucinations, confusion, psychotic-like behavior, disorientation, aggressive behavior, agitation, and delirium.

Ordinarily, patients with a major psychotic disorder should not be treated with carbidopa and levodopa orally disintegrating tablets, because of the risk of exacerbating psychosis. In addition, certain medications used to treat psychosis may exacerbate the symptoms of Parkinson’s disease and may decrease the effectiveness of carbidopa and levodopa orally disintegrating tablets.

Impulse Control / Compulsive Behaviors
Reports of patients taking dopaminergic medications (medications that increase central dopaminergic tone), suggest that patients may experience an intense urge to gamble, increased sexual urges, intense urges to spend money, binge eating, and/or other intense urges, and the inability to control these urges. In some cases, although not all, these urges were reported to have stopped when the dose was reduced or the medication was discontinued. Because patients may not recognize these behaviors as abnormal, it is important for prescribers to specifically ask patients or the caregivers about the development of new or increased gambling urges, sexual urges, uncontrolled spending or other urges while being treated with carbidopa and levodopa orally disintegrating tablets. Physicians should consider dose reduction or stopping the medication if a patient develops such urges while taking carbidopa and levodopa orally disintegrating tablets [see Information for Patients].

Melanoma
Epidemiological studies have shown that patients with Parkinson’s disease have a higher risk (2-to approximately 6-fold higher) of developing melanoma than the general population. Whether the increased risk observed was due to Parkinson’s disease or other factors, such as drugs used to treat Parkinson’s disease, is unclear.

For the reasons stated above, patients and providers are advised to monitor for melanomas frequently and on a regular basis when using carbidopa and levodopa orally disintegrating tablets for any indication. Ideally, periodic skin examinations should be performed by appropriately qualified individuals (e.g., dermatologists).

Information for Patients

Phenylketonuric patients should be informed that carbidopa and levodopa orally disintegrating tablets contain phenylalanine 3.37 mg per 10 mg/100 mg orally disintegrating tablet, 3.37 mg per 25 mg/100 mg orally disintegrating tablet, and 8.42 mg per 25 mg/250 mg orally disintegrating tablet.

Patients should be instructed not to remove carbidopa and levodopa orally disintegrating tablets from the bottle until just prior to dosing. With dry hands, the tablet should be gently removed and immediately placed on the tongue to dissolve and be swallowed with the saliva.

The patient should be informed that carbidopa and levodopa orally disintegrating tablet is an immediate-release formulation of carbidopa and levodopa that is designed to begin release of ingredients within 30 minutes. It is important that carbidopa and levodopa orally disintegrating tablets be taken at regular intervals according to the schedule outlined by the physician. The patient should be cautioned not to change the prescribed dosage regimen and not to add any additional antiparkinson medications, including other carbidopa and levodopa preparations, without first consulting the physician.

Patients should be advised that sometimes a ‘wearing-off’ effect may occur at the end of the dosing interval. The physician should be notified if such response poses a problem to lifestyle.

Patients should be advised that occasionally, dark color (red, brown, or black) may appear in saliva, urine, or sweat after ingestion of carbidopa and levodopa orally disintegrating tablets. Although the color appears to be clinically insignificant, garments may become discolored.
The patient should be advised that a change in diet to foods that are high in protein may delay the absorption of levodopa and may reduce the amount taken up in the circulation. Excessive acidity also delays stomach emptying, thus delaying the absorption of levodopa. Iron salts (such as in multivitamin tablets) may also reduce the amount of levodopa available to the body. The above factors may reduce the clinical effectiveness of the levodopa or carbidopa and levodopa therapy.

Patients should be alerted to the possibility of sudden onset of sleep during daily activities, in some cases without awareness or warning signs, when they are taking dopaminergic agents, including levodopa. Patients should be advised to exercise caution while driving or operating machinery and that if they have experienced somnolence and/or sudden sleep onset, they must refrain from these activities. (See WARNINGS, Falling Asleep During Activities of Daily Living and Somnolence.)

There have been reports of patients experiencing intense urges to gamble, increased sexual urges, and other intense urges, and the inability to control these urges while taking one or more of the medications that increase central dopaminergic tone and that are generally used for the treatment of Parkinson’s disease, including carbidopa and levodopa orally disintegrating tablets. Although it is not proven that the medications caused these events, these urges were reported to have stopped in some cases when the dose was reduced or the medication was stopped. Prescribers should ask patients about the development of new or increased gambling urges, sexual urges or other urges while being treated with carbidopa and levodopa orally disintegrating tablets. Patients should inform their physician if they experience new or increased gambling urges, increased sexual urges, or other intense urges while taking carbidopa and levodopa orally disintegrating tablets. Physicians should consider dose reduction or stopping the medication if a patient develops such urges while taking carbidopa and levodopa orally disintegrating tablets (See PRECAUTIONS, Impulse Control / Compulsive Behaviors).

Laboratory Tests

Abnormalities in laboratory tests may include elevations of liver function tests such as alkaline phosphatase, SGOT (AST), SGPT (ALT), lactic dehydrogenase (LDH), and bilirubin. Abnormalities in blood urea nitrogen (BUN) and positive Coombs test have also been reported. Commonly, levels of blood urea nitrogen, creatinine, and uric acid are lower during administration of carbidopa and levodopa than with levodopa.

Carbidopa and levodopa may cause a false-positive reaction for urinary ketone bodies when a test tape is used for determination of ketonuria. This reaction will not be altered by boiling the urine specimen. False-negative tests may result with the use of glucose-oxidase methods of testing for glucosuria.

Cases of falsely diagnosed pheochromocytoma in patients on carbidopa and levodopa therapy have been reported very rarely. Caution should be exercised when interpreting the plasma and urine levels of catecholamines and their metabolites in patients on levodopa or carbidopa and levodopa therapy.

Drug Interactions

Caution should be exercised when the following drugs are administered concomitantly with carbidopa and levodopa orally disintegrating tablets.

Symptomatic postural hypotension occurred when carbidopa and levodopa orally disintegrating tablets was added to the treatment of a patient receiving antihypertensive drugs. Therefore, when therapy with carbidopa and levodopa orally disintegrating tablets is started, dosage adjustment of the antihypertensive drug may be required.

For patients receiving MAO inhibitors (Type A or B), see CONTRAINDICATIONS. Concomitant therapy with selegiline and carbidopa and levodopa may be associated with severe orthostatic hypotension not attributable to carbidopa and levodopa alone (see CONTRAINDICATIONS).
There have been rare reports of adverse reactions, including hypertension and dyskinesia, resulting from the concomitant use of tricyclic antidepressants and carbidopa and levodopa orally disintegrating tablets.

Dopamine D2 receptor antagonists (e.g., phenothiazines, butyrophenones, risperidone) and isoniazid may reduce the therapeutic effects of levodopa. In addition, the beneficial effects of levodopa in Parkinson’s disease have been reported to be reversed by phenytoin and papaverine. Patients taking these drugs with carbidopa and levodopa orally disintegrating tablets should be carefully observed for loss of therapeutic response.

Use of carbidopa and levodopa orally disintegrating tablets with dopamine-depleting agents (e.g., reserpine and tetrabenazine) or other drugs known to deplete monoamine stores is not recommended.

Carbidopa and levodopa orally disintegrating tablets and iron salts or multivitamins containing iron salts should be coadministered with caution. Iron salts can form chelates with levodopa and carbidopa and consequently reduce the bioavailability of carbidopa and levodopa.
Although metoclopramide may increase the bioavailability of levodopa by increasing gastric emptying, metoclopramide may also adversely affect disease control by its dopamine receptor antagonistic properties.

Carcinogenesis, Mutagenesis, Impairment of Fertility

In a two-year bioassay of carbidopa and levodopa, no evidence of carcinogenicity was found in rats receiving doses of approximately two times the maximum daily human dose of carbidopa and four times the maximum daily human dose of levodopa.

In reproduction studies with carbidopa and levodopa, no effects on fertility were found in rats receiving doses of approximately two times the maximum daily human dose of carbidopa and four times the maximum daily human dose of levodopa.

Pregnancy

No teratogenic effects were observed in a study in mice receiving up to 20 times the maximum recommended human dose of carbidopa and levodopa. There was a decrease in the number of live pups delivered by rats receiving approximately two times the maximum recommended human dose of carbidopa and approximately five times the maximum recommended human dose of levodopa during organogenesis. Carbidopa and levodopa caused both visceral and skeletal malformations in rabbits at all doses and ratios of carbidopa/levodopa tested, which ranged from 10 times/5 times the maximum recommended human dose of carbidopa/levodopa to 20 times/10 times the maximum recommended human dose of carbidopa/levodopa.

There are no adequate or well-controlled studies in pregnant women. It has been reported from individual cases that levodopa crosses the human placental barrier, enters the fetus, and is metabolized. Carbidopa concentrations in fetal tissue appeared to be minimal. Use of carbidopa and levodopa orally disintegrating tablets in women of childbearing potential requires that the anticipated benefits of the drug be weighed against possible hazards to mother and child.

Nursing Mothers

Levodopa has been detected in human milk. Caution should be exercised when carbidopa and levodopa orally disintegrating tablets are administered to a nursing woman.

Pediatric Use

Safety and effectiveness in pediatric patients have not been established. Use of the drug in patients below the age of 18 is not recommended.

Geriatric Use

In the clinical efficacy trials for carbidopa and levodopa orally disintegrating tablets, almost half of the patients were older than 65, but few were older than 75. No overall meaningful differences in safety or effectiveness were observed between these subjects and younger subjects, but greater sensitivity of some older individuals to adverse drug reactions such as hallucinations cannot be ruled out. There is no specific dosing recommendation based upon clinical pharmacology data as carbidopa and levodopa orally disintegrating tablets are titrated as tolerated for clinical effect.

ADVERSE REACTIONS

The most common adverse reactions reported with carbidopa and levodopa orally disintegrating tablets have included dyskinesias, such as choreiform, dystonic, and other involuntary movements, and nausea.

The following other adverse reactions have been reported with carbidopa and levodopa:

Body as a Whole
Chest pain, asthenia.

Cardiovascular
Cardiac irregularities, hypotension, orthostatic effects including orthostatic hypotension, hypertension, syncope, phlebitis, palpitation.

Gastrointestinal
Dark saliva, gastrointestinal bleeding, development of duodenal ulcer, anorexia, vomiting, diarrhea, constipation, dyspepsia, dry mouth, taste alterations.

Hematologic
Agranulocytosis, hemolytic and non-hemolytic anemia, thrombocytopenia, leukopenia.

Hypersensitivity
Angioedema, urticaria, pruritus, Henoch-Schönlein purpura, bullous lesions (including pemphigus-like reactions).

Musculoskeletal
Back pain, shoulder pain, muscle cramps.

Nervous System/Psychiatric
Psychotic episodes including delusions, hallucinations, and paranoid ideation, bradykinetic episodes (“on-off” phenomenon), confusion, agitation, dizziness, somnolence, dream abnormalities including nightmares, insomnia, paresthesia, headache, depression with or without development of suicidal tendencies, dementia, pathological gambling, increased libido including hypersexuality, impulse control symptoms. Convulsions also have occurred; however, a causal relationship with carbidopa and levodopa has not been established.

Respiratory
Dyspnea, upper respiratory infection.

Skin
Rash, increased sweating, alopecia, dark sweat.

Urogenital
Urinary tract infection, urinary frequency, dark urine.

Laboratory Tests
Decreased hemoglobin and hematocrit; abnormalities in alkaline phosphatase, SGOT (AST), SGPT (ALT), LDH, bilirubin, BUN, Coombs test; elevated serum glucose; white blood cells, bacteria, and blood in the urine.

Other adverse reactions that have been reported with levodopa alone and with various carbidopa and levodopa formulations, and may occur with carbidopa and levodopa orally disintegrating tablets are:

Body as a Whole
Abdominal pain and distress, fatigue.

Cardiovascular
Myocardial infarction.

Gastrointestinal
Gastrointestinal pain, dysphagia, sialorrhea, flatulence, bruxism, burning sensation of the tongue, heartburn, hiccups.

Metabolic
Edema, weight gain, weight loss.

Musculoskeletal

Leg pain.

Nervous System/Psychiatric
Ataxia, extrapyramidal disorder, falling, anxiety, gait abnormalities, nervousness, decreased mental acuity, memory impairment, disorientation, euphoria, blepharospasm (which may be taken as an early sign of excess dosage; consideration of dosage reduction may be made at this time), trismus, increased tremor, numbness, muscle twitching, activation of latent Horner’s syndrome, peripheral neuropathy.

Respiratory
Pharyngeal pain, cough.

Skin
Malignant melanoma, flushing.

Special Senses
Oculogyric crises, diplopia, blurred vision, dilated pupils.

Urogenital
Urinary retention, urinary incontinence, priapism.

Miscellaneous
Bizarre breathing patterns, faintness, hoarseness, malaise, hot flashes, sense of stimulation.

Laboratory Tests
Decreased white blood cell count and serum potassium; increased serum creatinine and uric acid; protein and glucose in urine.

To report SUSPECTED ADVERSE REACTIONS, contact Rising Pharma Holdings, Inc. at 1-844-874-7464 or FDA at 1-800-FDA-1088 or www.fda.gov/medwatch.

OVERDOSAGE

Management of acute overdosage with carbidopa and levodopa orally disintegrating tablets is the same as management of acute overdosage with levodopa. Pyridoxine is not effective in reversing the actions of carbidopa and levodopa orally disintegrating tablets.

General supportive measures should be employed, along with immediate gastric lavage. Intravenous fluids should be administered judiciously and an adequate airway maintained. Electrocardiographic monitoring should be instituted and the patient carefully observed for the development of arrhythmias; if required, appropriate antiarrhythmic therapy should be given. The possibility that the patient may have taken other drugs as well as carbidopa and levodopa orally disintegrating tablets should be taken into consideration. To date, no experience has been reported with dialysis; hence, its value in overdosage is not known.

Based on studies in which high doses of levodopa and/or carbidopa were administered, a significant proportion of rats and mice given single oral doses of levodopa of approximately 1500 to 2000 mg/kg are expected to die. A significant proportion of infant rats of both sexes are expected to die at a dose of 800 mg/kg. A significant proportion of rats are expected to die after treatment with similar doses of carbidopa. The addition of carbidopa in a 1:10 ratio with levodopa increases the dose at which a significant proportion of mice are expected to die to 3360 mg/kg.

DOSAGE AND ADMINISTRATION

Instructions for Use/Handling Carbidopa and Levodopa Orally Disintegrating Tablets:

Just prior to administration, GENTLY remove the tablet from the bottle with dry hands. IMMEDIATELY place the carbidopa and levodopa orally disintegrating tablet on top of the tongue where it will dissolve in seconds, then swallow with saliva. Administration with liquid is not necessary.

The optimum daily dosage of carbidopa and levodopa orally disintegrating tablets must be determined by careful titration in each patient. carbidopa and levodopa orally disintegrating tablets are available in a 1:4 ratio of carbidopa to levodopa (carbidopa and levodopa orally disintegrating tablets 25 mg/100 mg) as well as 1:10 ratio (carbidopa and levodopa orally disintegrating tablets 25 mg/250 mg and carbidopa and levodopa orally disintegrating tablets 10 mg/100 mg). Tablets of the two ratios may be given separately or combined as needed to provide the optimum dosage.

Studies show that peripheral dopa decarboxylase is saturated by carbidopa at approximately 70 to 100 mg a day. Patients receiving less than this amount of carbidopa are more likely to experience nausea and vomiting.

Usual Initial Dosage

Dosage is best initiated with one tablet of carbidopa and levodopa orally disintegrating tablets 25 mg/100 mg three times a day. This dosage schedule provides 75 mg of carbidopa per day. Dosage may be increased by one tablet every day or every other day, as necessary, until a dosage of eight tablets of carbidopa and levodopa orally disintegrating tablets 25 mg/100 mg a day is reached.

If carbidopa and levodopa orally disintegrating tablets 10 mg/100 mg is used, dosage may be initiated with one tablet three or four times a day. However, this will not provide an adequate amount of carbidopa for many patients. Dosage may be increased by one tablet every day or every other day until a total of eight tablets (2 tablets q.i.d.) is reached.

How to Transfer Patients from Levodopa

Levodopa must be discontinued at least twelve hours before starting carbidopa and levodopa orally disintegrating tablets. A daily dosage of carbidopa and levodopa orally disintegrating tablets should be chosen that will provide approximately 25% of the previous levodopa dosage. Patients who are taking less than 1500 mg of levodopa a day should be started on one tablet of carbidopa and levodopa orally disintegrating tablets 25 mg/100 mg three or four times a day. The suggested starting dosage for most patients taking more than 1500 mg of levodopa is one tablet of carbidopa and levodopa orally disintegrating tablets 25 mg/250 mg three or four times a day.

Maintenance

Therapy should be individualized and adjusted according to the desired therapeutic response. At least 70 to 100 mg of carbidopa per day should be provided. When a greater proportion of carbidopa is required, one tablet of carbidopa and levodopa orally disintegrating tablets 25 mg/100 mg may be substituted for each tablet of carbidopa and levodopa orally disintegrating tablets 10 mg/100 mg. When more levodopa is required, carbidopa and levodopa orally disintegrating tablets 25 mg/250 mg should be substituted for carbidopa and levodopa orally disintegrating tablets 25 mg/100 mg or carbidopa and levodopa orally disintegrating tablets 10 mg/100 mg. If necessary, the dosage of carbidopa and levodopa 25 mg/250 mg may be increased by one-half or one tablet every day or every other day to a maximum of eight tablets a day. Experience with total daily dosages of carbidopa greater than 200 mg is limited.

Because both therapeutic and adverse responses occur more rapidly with carbidopa and levodopa orally disintegrating tablets than with levodopa alone, patients should be monitored closely during the dose adjustment period. Specifically, involuntary movements will occur more rapidly with carbidopa and levodopa orally disintegrating tablets than with levodopa. The occurrence of involuntary movements may require dosage reduction. Blepharospasm may be a useful early sign of excess dosage in some patients.

Addition of Other Antiparkinsonian Medications

Standard drugs for Parkinson’s disease, other than levodopa without a decarboxylase inhibitor, may be used concomitantly while carbidopa and levodopa orally disintegrating tablets are being administered, although dosage adjustments may be required.

Interruption of Therapy

Sporadic cases of hyperpyrexia and confusion have been associated with dose reductions and withdrawal of carbidopa and levodopa. Patients should be observed carefully if abrupt reduction or discontinuation of carbidopa and levodopa orally disintegrating tablets is required, especially if the patient is receiving neuroleptics. (See WARNINGS.)

If general anesthesia is required, carbidopa and levodopa orally disintegrating tablets may be continued as long as the patient is permitted to take fluids and medication by mouth. If therapy is interrupted temporarily, the patient should be observed for symptoms resembling NMS, and the usual daily dosage may be administered as soon as the patient is able to take oral medication.

HOW SUPPLIED

Carbidopa and Levodopa Orally Disintegrating Tablets, USP are available containing 10 mg or 25 mg of carbidopa, USP, with 100 mg or 250 mg of levodopa, USP providing the following available combinations: 10 mg/100 mg, 25 mg/100 mg or 25 mg/250 mg.

The 10 mg/100 mg orally disintegrating tablet is a green, round, flat-faced, beveled edge tablet debossed with R above the score and A12 below the score on one side of the tablet and plain on the other side. They are available as follows:

NDC 16571-157-01……….……bottles of 100 tablets

The 25 mg/100 mg orally disintegrating tablet is a blue, round, flat-faced, beveled edge tablet debossed with R above the score and A13 below the score on one side of the tablet and plain on the other side. They are available as follows:

NDC 16571-158-01……………bottles of 100 tablets

The 25 mg/250 mg orally disintegrating tablet is a green, round, flat-faced, beveled edge tablet debossed with R above the score and A14 below the score on one side of the tablet and plain on the other side. They are available as follows:

NDC 16571-159-01…………...bottles of 100 tablets

Store at 20º to 25ºC (68º to 77ºF); excursions permitted to 15° to 30°C (59° to 86°F) [See USP Controlled Room Temperature].

Protect from moisture and light.

Dispense in a tight, light-resistant container as defined in the USP using a child-resistant closure.

Manufactured for:
Rising Pharma Holdings, Inc.
East Brunswick, NJ 08816

Made in India

Neutral Code: 4323066/TS/DRUGS/2025

Revised: 01/2026

PIR15901-04

PRINCIPAL DISPLAY PANEL - 10 mg/100 mg

PACKAGE LABEL-PRINCIPAL DISPLAY PANEL - 10 mg/100 mg (100 Tablets)

Rising Pharmaceuticals
NDC 16571-157-01
Carbidopa and Levodopa Orally Disintegrating Tablets, USP
10 mg/100 mg

Phenylketonurics: Contains phenylalanine
3.37 mg per tablet.

Rx only

100 Tablets

PRINCIPAL DISPLAY PANEL - 25 mg/100 mg

PACKAGE LABEL-PRINCIPAL DISPLAY PANEL - 25 mg/100 mg (100 Tablets)
Rising Pharmaceuticals
NDC 16571-158-01
Carbidopa and Levodopa Orally Disintegrating Tablets, USP
25mg/100 mg

Phenylketonurics: Contains phenylalanine
3.37 mg per tablet.

Rx only

100 Tablets

PRINCIPAL DISPLAY PANEL - 25 mg/250 mg

PACKAGE LABEL-PRINCIPAL DISPLAY PANEL - 25 mg/250 mg (100 Tablets)
Rising Pharmaceuticals
NDC 16571-159-01
Carbidopa and Levodopa Orally Disintegrating Tablets, USP
25 mg/250 mg

Phenylketonurics: Contains phenylalanine
8.42 mg per tablet.

Rx only

100 Tablets